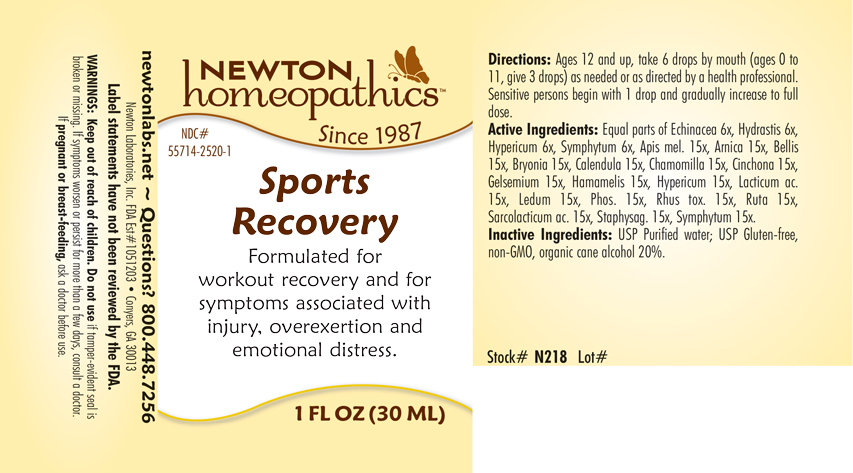 DRUG LABEL: Sports Recovery
NDC: 55714-2520 | Form: LIQUID
Manufacturer: Newton Laboratories, Inc.
Category: homeopathic | Type: HUMAN OTC DRUG LABEL
Date: 20250210

ACTIVE INGREDIENTS: ECHINACEA, UNSPECIFIED 6 [hp_X]/1 mL; APIS MELLIFERA 15 [hp_X]/1 mL; ARNICA MONTANA 15 [hp_X]/1 mL; BELLIS PERENNIS 15 [hp_X]/1 mL; BRYONIA ALBA ROOT 15 [hp_X]/1 mL; CALENDULA OFFICINALIS FLOWERING TOP 15 [hp_X]/1 mL; MATRICARIA CHAMOMILLA 15 [hp_X]/1 mL; CINCHONA OFFICINALIS BARK 15 [hp_X]/1 mL; GELSEMIUM SEMPERVIRENS ROOT 15 [hp_X]/1 mL; HAMAMELIS VIRGINIANA ROOT BARK/STEM BARK 15 [hp_X]/1 mL; HYPERICUM PERFORATUM 15 [hp_X]/1 mL; LACTIC ACID, DL- 15 [hp_X]/1 mL; RHODODENDRON TOMENTOSUM LEAFY TWIG 15 [hp_X]/1 mL; PHOSPHORUS 15 [hp_X]/1 mL; TOXICODENDRON PUBESCENS LEAF 15 [hp_X]/1 mL; RUTA GRAVEOLENS FLOWERING TOP 15 [hp_X]/1 mL; LACTIC ACID, L- 15 [hp_X]/1 mL; DELPHINIUM STAPHISAGRIA SEED 15 [hp_X]/1 mL; COMFREY ROOT 15 [hp_X]/1 mL; GOLDENSEAL 6 [hp_X]/1 mL
INACTIVE INGREDIENTS: WATER; ALCOHOL

Sports 2520L

INDICATIONS & USAGE SECTION

Formulated for workout recovery and for symptoms associated with injury, overexertion and emotional distress.

OTC - ACTIVE INGREDIENT SECTION

Equal parts of Echinacea 6x, Hydrastis canadensis 6x, Hypericum perforatum 6x, Symphytum officinale 6x, Apis mellifica 15x, Arnica montana 15x, Bellis perennis 15x, Bryonia 15x, Calendula officinalis 15x, Chamomilla 15x, Cinchona officinalis 15x, Gelsemium sempervirens 15x, Hamamelis virginiana 15x, Hypericum perforatum 15x, Lacticum acidum 15x, Ledum palustre 15x, Phosphorus 15x, Rhus toxicodendron 15x, Ruta graveolens 15x, Sarcolacticum acidum 15x, Staphysagria 15x, Symphytum officinale 15x.

OTC - PURPOSE SECTION

Formulated for workout recovery and for symptoms associated with injury, overexertion and emotional distress.

INACTIVE INGREDIENT SECTION

USP Purified Water; USP Gluten-free, non-GMO, organic cane alcohol 20%.

QUESTIONS SECTION

newtonlabs.net – Questions? 800.448.7256

Newton Laboratories, Inc. FDA Est # 1051203 - Conyers, GA 30013

WARNINGS SECTION

WARNINGS: Keep out of reach of children. Do not use if tamper-evident seal is broken or missing. If symptoms worsen or persist for more than a few days, consult a doctor. If pregnant or breast-feeding, ask a doctor before use.

OTC - PREGNANCY OR BREAST FEEDING SECTION

If pregnant or breast-feeding, ask a doctor before use.

OTC - KEEP OUT OF REACH OF CHILDREN SECTION

Keep out of reach of children.

DOSAGE & ADMINISTRATION SECTION

Directions: Ages 12 and up, take 6 drops by mouth (ages 0 to 11, give 3 drops) as need or as directed by a health professional. Sensitive person begin with 1 drop and gradually increase to full dose.